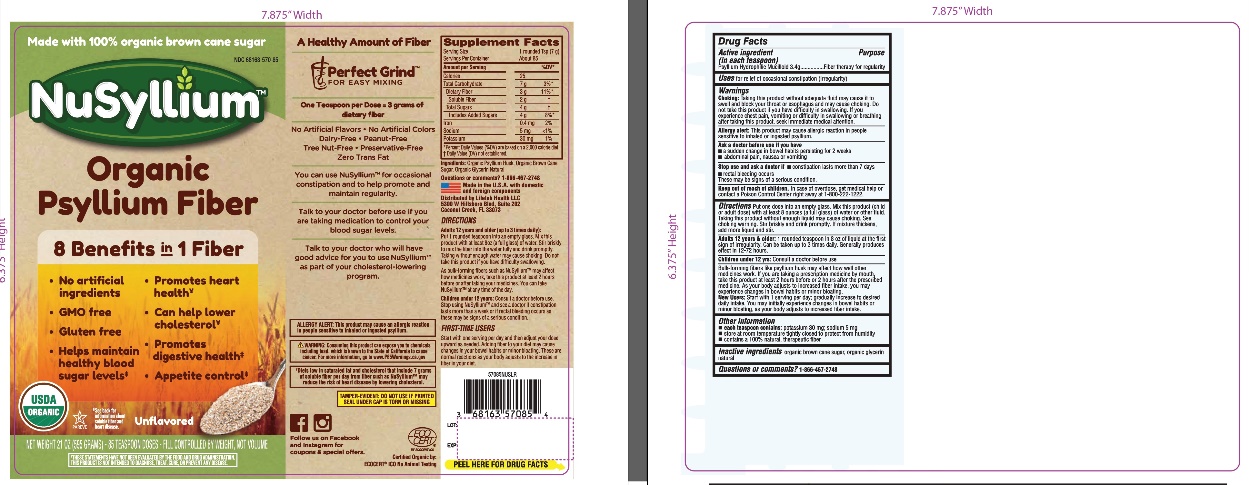 DRUG LABEL: Unflavored Organic Natural Fiber
NDC: 68163-570 | Form: POWDER
Manufacturer: Raritan Pharmaceuticals Inc
Category: otc | Type: HUMAN OTC DRUG LABEL
Date: 20250130

ACTIVE INGREDIENTS: PSYLLIUM HUSK 3.4 g/7 g
INACTIVE INGREDIENTS: RAW SUGAR; GLYCERIN

Supplement Facts

Serving Size | 1 rounded teaspoon (7g)
Servings per Container | About 85
Amount Per Serving |  | %DV*
Calories | 25
Total Carbohydrate | 7 g | 3%
Dietary Fiber | 3g | 11%
Soluble Fiber | 2g | †
Total Sugars | 4g | †

Includes Added Sugars 4g 8%

Iron | 0.4mg | 2%
Sodium | 5mg | <1%
Potassium | 30 mg | 1%

*Percent Daily Values (%DV) are based on a 2000 calorie diet,

† Daily Value (DV) not established

Purpose

Bulk-forming laxative

Use

For relief of occasional constipation (regularity)

Warnings

Choking: Taking this product without adequate fluid may cause it to swell and block your throat or esophagus and may cause choking. Do not take this product, if you have difficulty in swallowing.

If you experience chest pain, vomiting or difficulty in swallowing or breathing after taking this product, seek immediate medical attention.

Allergy alert: This product may cause an allergic reaction in people sensitive to inhaled or ingested psyllium.

Safety Warning

TAMPER-EVIDENT: DO NOT USE IF PRINTED SEAL UNDER CAP IS TORN OR MISSING

Directions

Put one dose into an empty glass. Mix this product (child or adult dose) with at least 8 ounces (a full glass) of water or other fluid. Taking this product without enough liquid may cause choking. See choking warning. Stir briskly and drink promptly.

If mixture thickens, add more liquid.

Adults 12 Years and older: 1 rounded TEASPOON into an 8 oz of liquid at the first sign of irregularity. Can be taken up to 3 times daily. Generally produces effect in 12-72 hours.

Children under 12 years: Consult a doctor before use.

Bulk-forming fibers like Psyllium husk may affect how well other medicines work, If you are taking a prescription medicine by mouth, take this product at least 2 hours before or after the prescribed medicine.

As your body adjusts to increased fiber intake, you may experience changes in bowel habits or minor bloating.

NEW USERS

Start with 1 serving per day; gradually increase to desired daily intake. You may initially experience changes in bowel habits or minor bloating as your body adjusts to increased fiber intake.

Other information

- each teaspoon contains: potassium 35 mg; sodium 5 mg
- store at room temperature tightly closed to protect from humidity
- do not use if printed seal under cap is torn or missing
- contains a 100% natural, therapeutic fiber

‡ Diets low in saturated fat and cholesterol that include 7 grams of soluble fiber per day from fiber such as NuSyllium may reduce the risk of heart disease by lowering cholesterol.

*These statements have not been evaluated by the Food and Drug Administration. This product is not intended to diagnose, treat, cure or prevent any disease.

ALLERGY ALERT: This product may cause an allergic reaction in people sensitive to inhaled or ingested psyllium.

Questions or comments?

1-866-467-2748

Inactive ingredients

Organic Brown Cane Sugar, Organic Vegetable Glycerin.

Principal Display Panel

NDC 68163-570-85

NuSyllium

Unflavored Organic Natural Fiber

100% Organic Certified Psyllium

Perfect Grind For Easy Mixing™

USDA ORGANIC

NO ARTIFICIAL INGREDIENTS

100% Natural Fiber Supplement

Fiber Laxative for Regularity

Made with 100% Organic Brown Cane Sugar

Folks are taking about the Benefits of NuSyllium Ultra Organic Natural Fiber!

- You can use NuSyllium to feel less hungry between meals.
- Maintain healthy blood sugar levels by using NuSyllium Ultra as part of your sugar free diet*. Talk to your doctor before use if you are taking medication to control your blood sugar levels.
- Organic NuSyllium is a great choice for promoting and maintain digestive health. You can use NuSyllium Ultra for occasional constipation and to help promote and maintain regularity.
- Did you know that one dose of NuSyllium Ultra contains 2 gm. of soluble fiber? You can use it for lowering cholesterol and promoting heart health*.
- Talk to your doctor who will have good advice for you to use NuSyllium Ultra as part of your cholesterol –lowering program.

No Artificial Flavors, Peanut-free

No Artificial Colors, Tree Nut-free

GMO-free, Preservative-free

Gluten-free, Zero Trans Fat

Diary-free, No animal testing

NET WT 21 OZ (595 g) 85 DOSES

Fill controlled by weight, not volume

Made in the U.S.A. with domestic and foreign components.

Distributed by: Lifelab Health LLC

6574 N.State Road #7 361

Coconut Creek, FL 33073, No animal testing